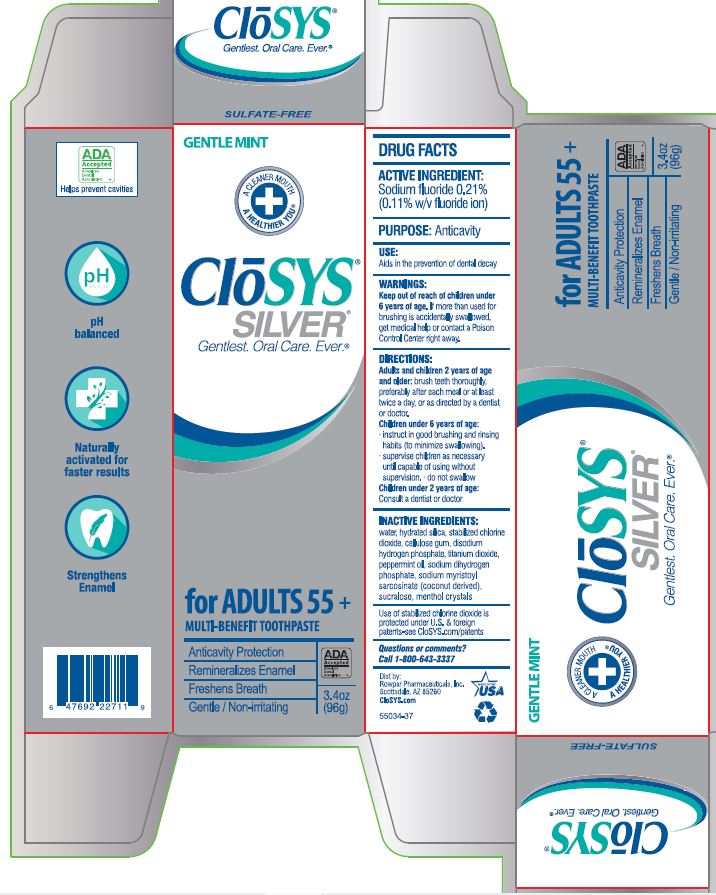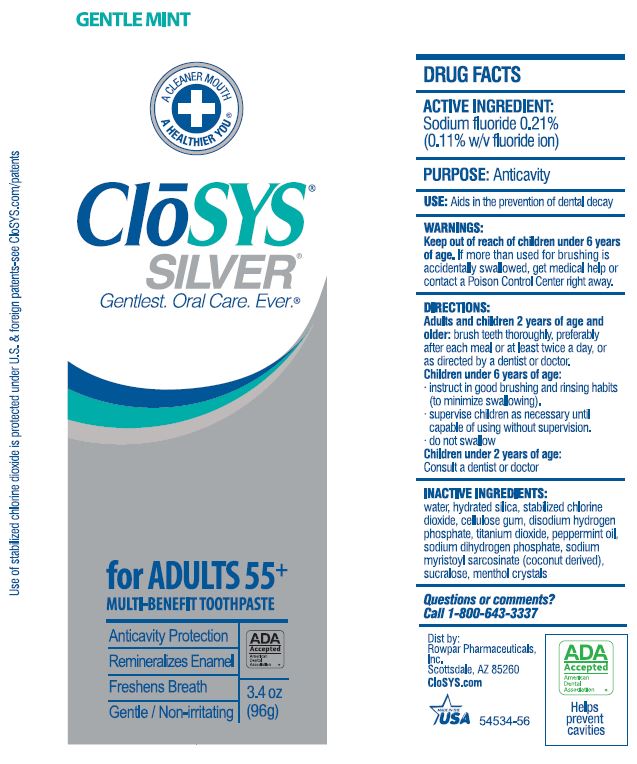 DRUG LABEL: CloSYS
NDC: 58578-0759 | Form: PASTE, DENTIFRICE
Manufacturer: Rowpar Pharmaceuticals, Inc.
Category: otc | Type: HUMAN OTC DRUG LABEL
Date: 20250516

ACTIVE INGREDIENTS: SODIUM FLUORIDE 0.916 mg/1 g
INACTIVE INGREDIENTS: WATER; HYDRATED SILICA; CHLORINE DIOXIDE; CARBOXYMETHYLCELLULOSE; SODIUM PHOSPHATE, DIBASIC, ANHYDROUS; TITANIUM DIOXIDE; PEPPERMINT OIL; SODIUM PHOSPHATE, MONOBASIC, ANHYDROUS; SODIUM MYRISTOYL SARCOSINATE; SUCRALOSE; MENTHOL, UNSPECIFIED FORM

CloSYS® SILVER Gentle Fluoride TOOTHPASTE

ACTIVE INGREDIENT:

Sodium fluoride 0.21% (0.11% w/v fluoride ion)

PURPOSE:

Anticavity

USES:

aids in the prevention of dental decay

WARNINGS:

Keep out of reach of children under 6 years of age. If more than used for brushing is accidentally swallowed, get medical help or contact a Poison Control Center right away.

DIRECTIONS:

Adults and children 2 years of age and older: brush teeth thoroughly, preferably after each meal or at least twice a day, or as directed by a dentist or doctor.
Children under 6 years of age:
· instruct in good brushing and rinsing habits (to minimize swallowing).
· supervise children as necessary until capable of using without supervision.
· do not swallow
Children under 2 years of age:
Consult a dentist or doctor

INACTIVE INGREDIENTS:

water, hydrated silica, stabilized chlorine dioxide, cellulose gum, disodium hydrogen phosphate, titanium dioxide, peppermint oil, sodium dihydrogen phosphate, sodium myristoyl sarcosinate (coconut derived), sucralose, menthol crystals

Questions or comments?

Call 1-800-643-3337

Packaging

GENTLE MINT
A CLEANER MOUTH
A HEALTHIER YOU®
CLōSYS®
SILVER®
Gentlest. Oral Care. Ever®
for ADULTS 55+
MULTI-BENEFIT TOOTHPASTE
Anticavity Protection
Remineralizes Enamel
Freshens Breath
Gentle / Non-irritating
ADA Accepted
American Dental Association
3.4 oz
(96g)
ADA Accepted
American Dental Association
Helps prevent cavities
pH balanced
Naturally activated for faster results
Strengthens Enamel
SULFATE-FREE
Dist by:
Rowpar Pharmaceutical, Inc.
Scottsdale, AZ 85260
CloSYS.com
55034-37
MADE IN THE
USA

GENTLE MINT
A CLEANER MOUT
A HEALTHIER YOU®
CLōSYS® SILVER®
Gentlest. Oral Care. Ever®
for ADULTS 55+
MULTI-BENEFIT TOOTHPASTE
Anticavity Protection
Remineralizes Enamel
Freshens Breath
Gentle / Non-irritating
3.4 oz
(96g)
Use of standardized chlorine dioxide is protected under U.S. & foreign patents-see CloSYS.com/patents
ADA Accepted
American Dental Association
Helps prevent cavities
Dist by:
Rowpar Pharmaceutical, Inc.
Scottsdale, AZ 85260
CloSYS.com
MADE IN THE
USA
54534-56